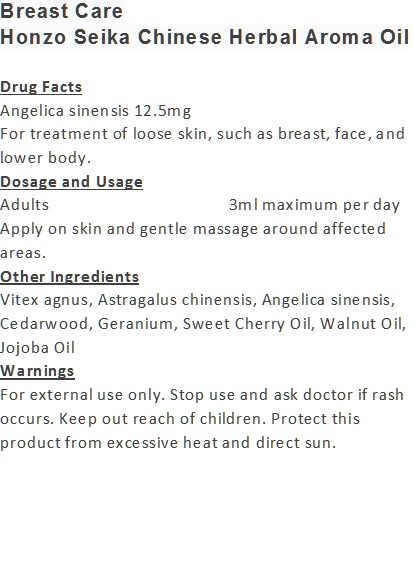 DRUG LABEL: Breast Care
NDC: 71263-9905 | Form: OIL
Manufacturer: NIC CO., LTD.
Category: otc | Type: HUMAN OTC DRUG LABEL
Date: 20170101

ACTIVE INGREDIENTS: ANGELICA SINENSIS ROOT 12.5 mg/100 mL
INACTIVE INGREDIENTS: CEDRUS ATLANTICA BARK OIL; SWEET CHERRY SEED OIL; WALNUT OIL; JOJOBA OIL; VITEX AGNUS-CASTUS WHOLE; ASTRAGALUS CHINENSIS SEED; GERANIUM OIL, ALGERIAN TYPE

Drug Facts

Angelica sinensis 12.5mg

Use

For treatment of loose skin, such as breast, face, and lower body.

Dosage Suggestion

Adults 3ml maximum per day

INACTIVE INGREDIENT

Other Ingredients

Vitex agnus, Astragalus chinensis, Cedarwood, Geranium, Sweet Cherry Oil, Walnut Oil, Jojoba Oil

Directions

Apply on skin and gentle massage around affected area.

Warnings

For external use only. Stop use and ask doctor if rash occurs. Keep out reach of children.

Other Information

Protect this product from excessive heat

and direct sun.

Warnings

For external use only. Stop use and ask doctor if rash occurs. Keep out reach of children.